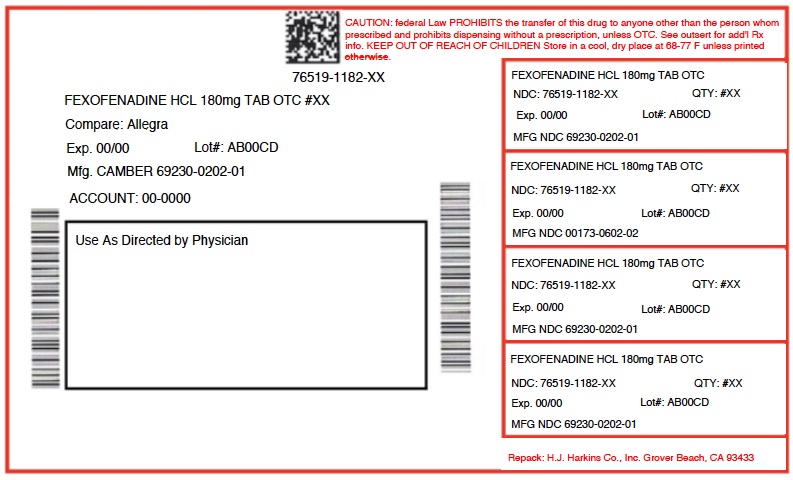 DRUG LABEL: FEXOFENADINE HCL
NDC: 76519-1182 | Form: TABLET, FILM COATED
Manufacturer: H.J. Harkins Company, Inc.
Category: otc | Type: HUMAN OTC DRUG LABEL
Date: 20190628

ACTIVE INGREDIENTS: FEXOFENADINE HYDROCHLORIDE 180 mg/1 1
INACTIVE INGREDIENTS: SILICON DIOXIDE; LACTOSE MONOHYDRATE; HYPROMELLOSES; STARCH, CORN; CROSCARMELLOSE SODIUM; STEARIC ACID; TITANIUM DIOXIDE; FERRIC OXIDE YELLOW; FERRIC OXIDE RED; ANHYDROUS LACTOSE; POLYETHYLENE GLYCOL, UNSPECIFIED

1182 FEXOFENADINE HCL

ACTIVE INGREDIENT

Fexofenadine HCl USP, 180 mg

PURPOSE

Antihistamine

DOSAGE AND ADMINISTRATION

adults and children 12 years of age and over | take one 180mg tablet with water once a day; do not take more than 1 tablet in 24 hours
children under 12 years of age | do not use
adults 65 years of age and older | ask a doctor
consumers with kidney disease | ask a doctor

Do not use

if you have ever had an allergic reaction to this product or any of its ingredients.

Ask a doctor before use if you have

kidney disease. Your doctor should determine if you need a different dose.

When using this product

- do not take more than directed
- do not take at the same time as aluminum or magnesium antacids
- do not take with fruit juices (see Directions)

Stop use and ask a doctor if

an allergic reaction to this product occurs. Seek medical help right away.

If pregnant or breast-feeding,

ask a health professional before use.

OTHER SAFETY INFORMATION

- safety sealed: do not use if carton is opened or if printed foil inner seal on bottle is torn or missing
- store between 20° and 25°C (68° and 77°F)
- protect from excessive moisture
- each tablet contains: sodium 8.2 mg
- this product meets the requirements of USP Dissolution Test 2

INACTIVE INGREDIENT

anhydrous lactose, colloidal silicon dioxide, corn starch, croscarmellose sodium, lactose monohydrate, pregelatinized starch (maize), stearic acid, opadry pink 03B84893 containing hypromellose, polyethylene glycol, red iron oxide, titanium dioxide and yellow iron oxide.

Keep out of reach of children.

In case of overdose, get medical help or contact a Poison Control Center right away.

INDICATIONS AND USAGE

temporarily relieves these symptoms due to hay fever or other upper respiratory allergies:

- runny nose
- itchy, watery eyes
- sneezing
- itching of the nose or throat